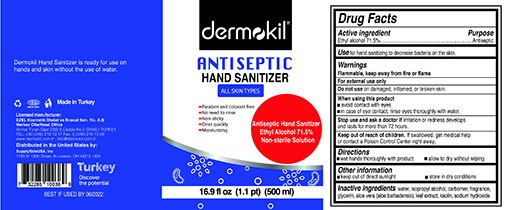 DRUG LABEL: Dermokil
NDC: 75004-786 | Form: GEL
Manufacturer: Halshe, LLC
Category: otc | Type: HUMAN OTC DRUG LABEL
Date: 20200402

ACTIVE INGREDIENTS: ALCOHOL 71.5 mL/100 mL
INACTIVE INGREDIENTS: SODIUM HYDROXIDE 0.01 mL/100 mL; ISOPROPYL ALCOHOL 2 mL/100 mL; GLYCERIN; WATER

Active Ingredient(s)

Ethyl Alcohol 71.5% v/v. Purpose: Antiseptic

Purpose

Antiseptic, Hand Sanitizer

Warnings

For external use only. Flammable. Keep away from heat or flame

Do not use on damaged, inflamed or broken skin

When using this product

Avoid contact with eyes

In case of eye contact, rinse eyes thoroughly with water

Stop use

Stop use and ask a doctor if irritation or redness develops and lasts for more than 72 hours.

Keep out of reach of children. If swallowed, get medical help or contact a Poison Control Center right away.

Directions

- wet hands thoroughly with product

- allow to dry without wiping

Other information

- keep out of direct sunlight

- store in dry conditions

Inactive ingredients

glycerin, isopropyl alcohol, sodium hydroxide, purified water USP

Use

Use for hand sanitizing to decrease bacteria on the skin

Package Label - Principal Display Panel

500 ml NDC: 75004-786-55